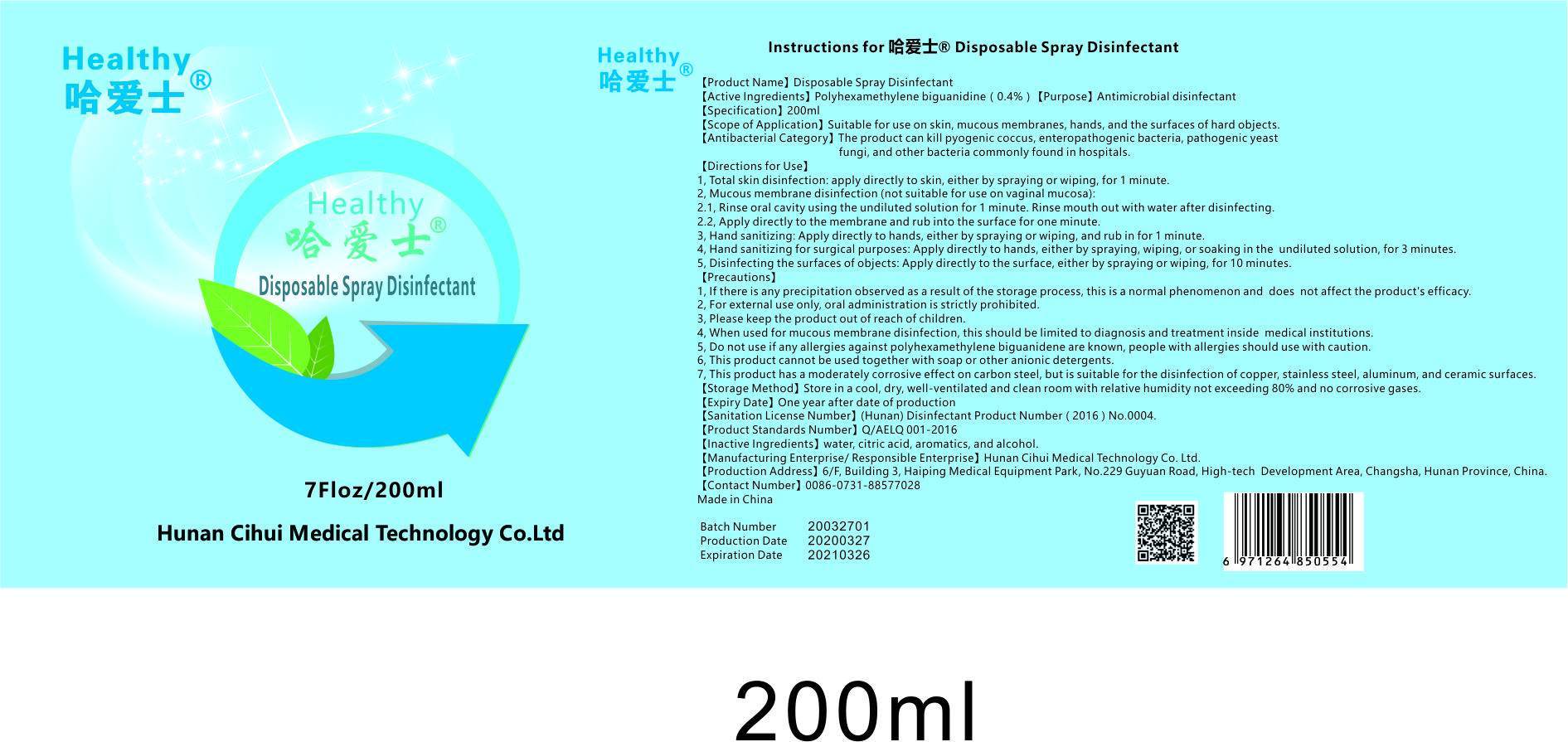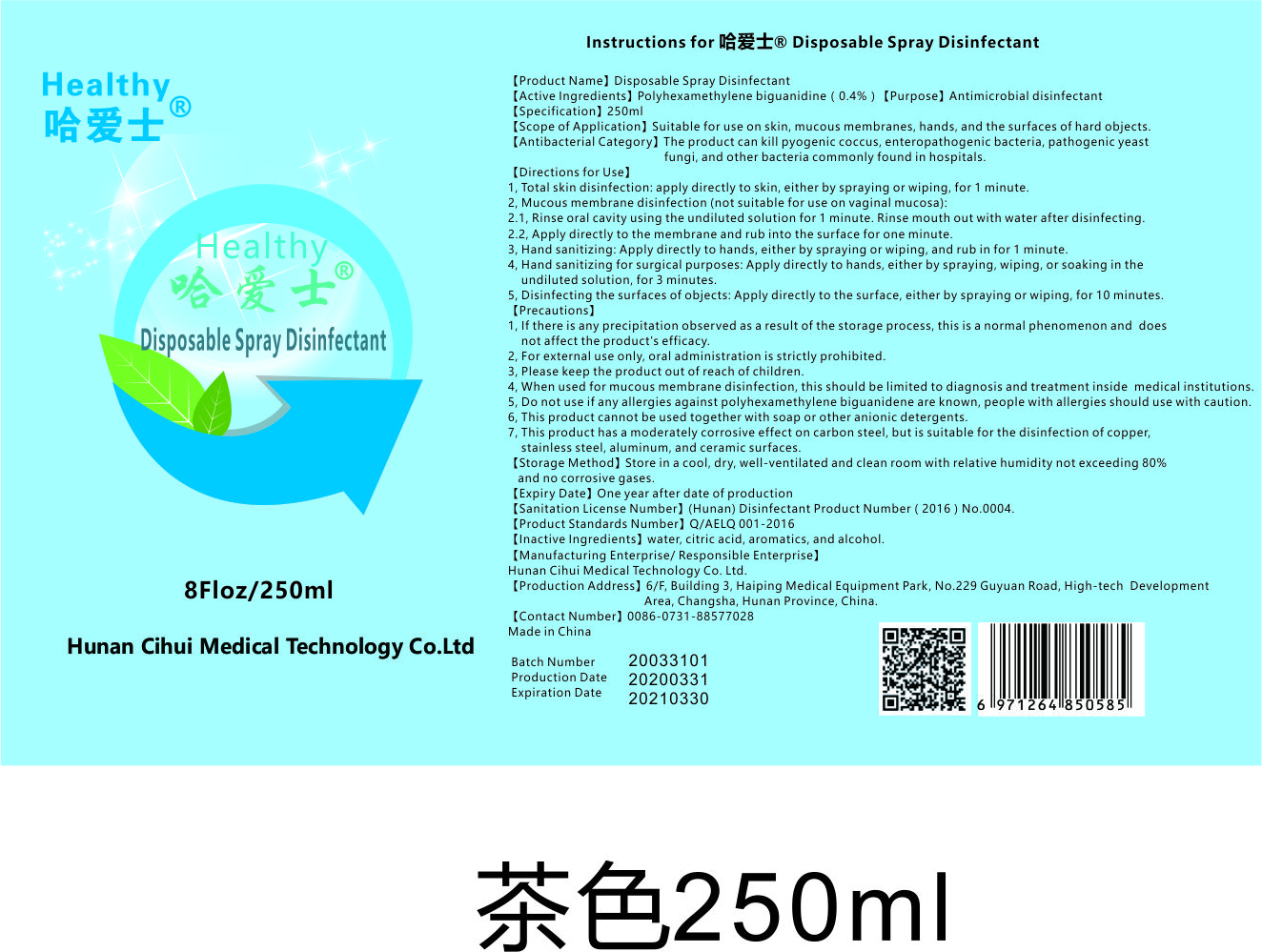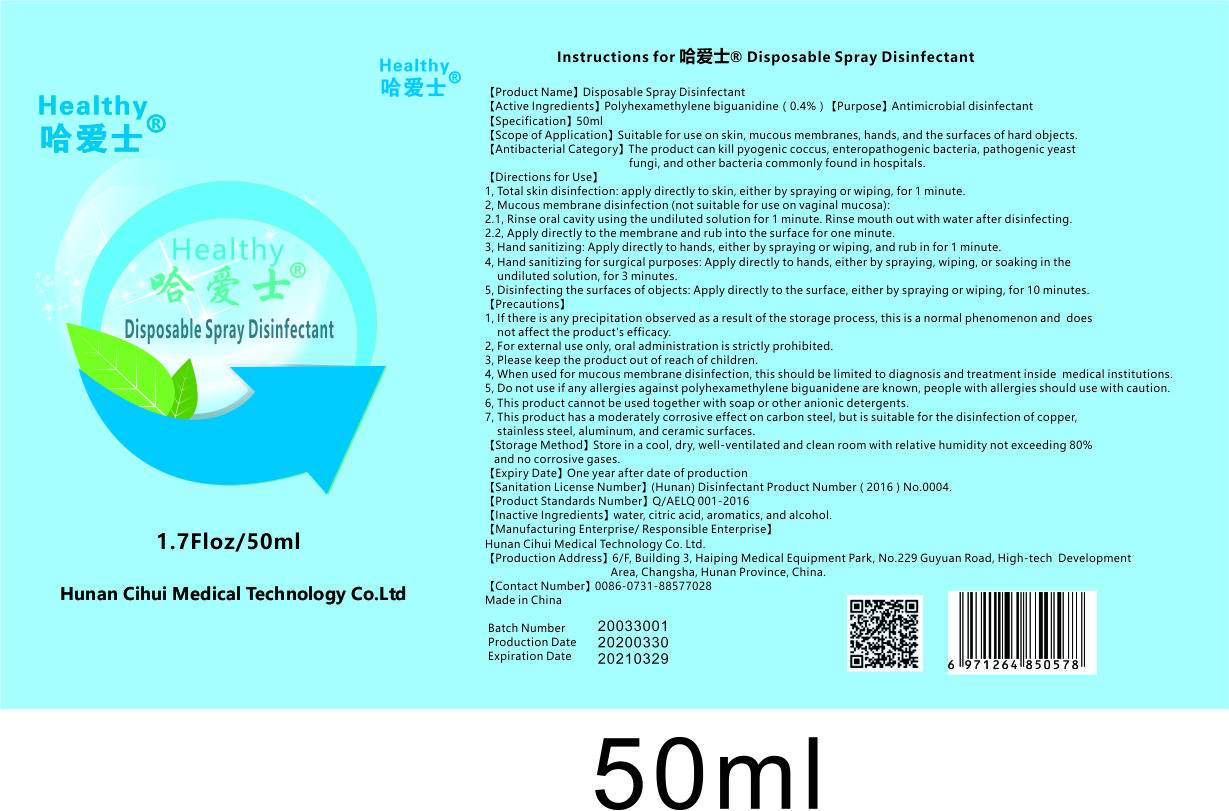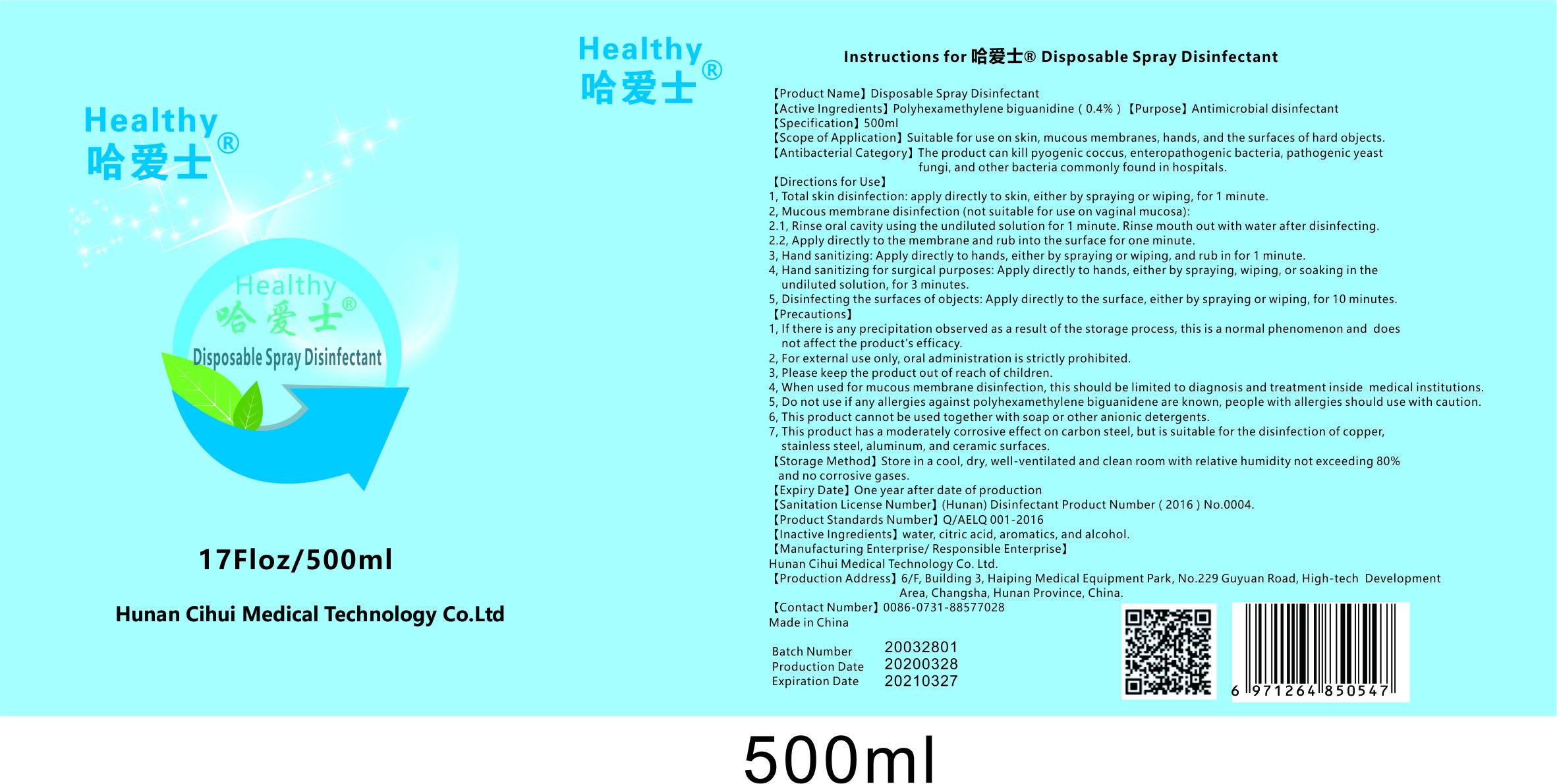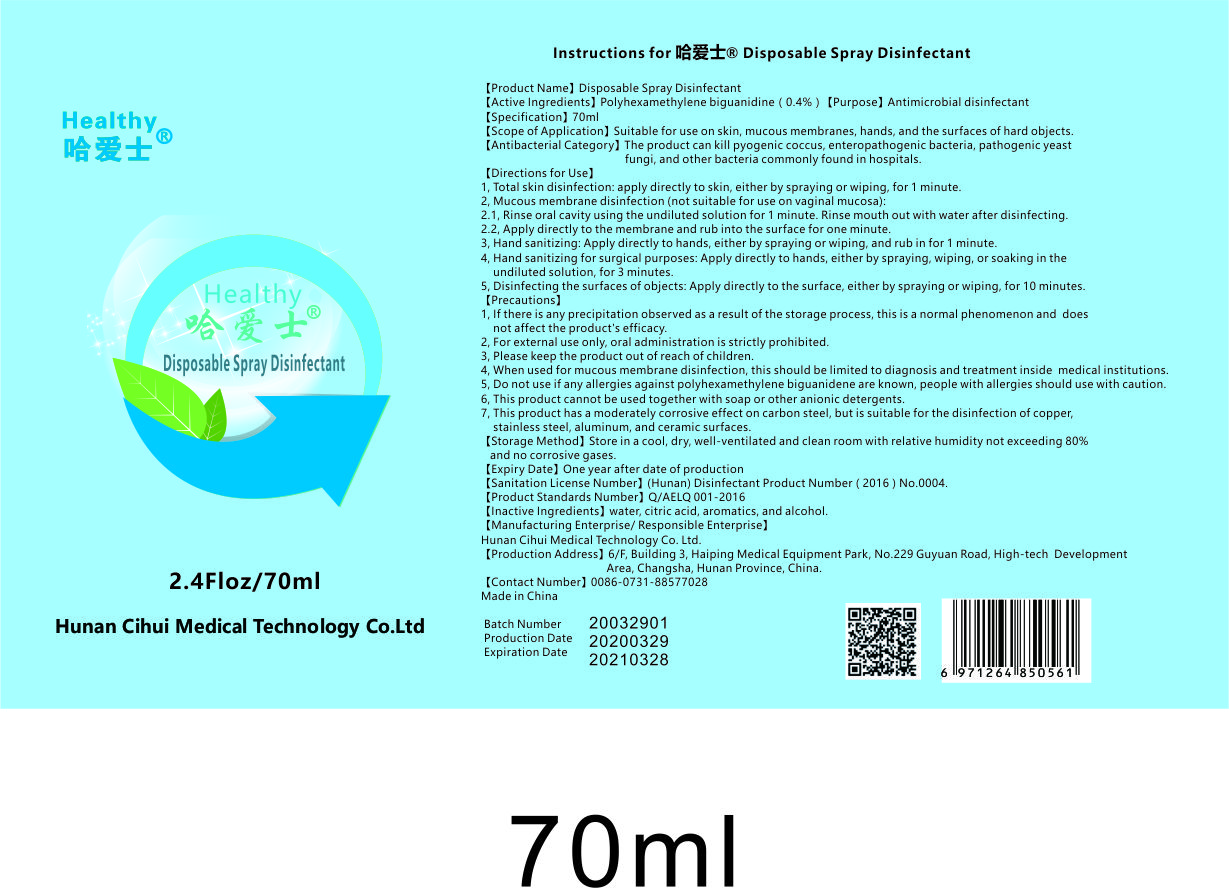 DRUG LABEL: Disposable Disinfectant
NDC: 74762-001 | Form: SPRAY
Manufacturer: Hunan Cihui Medical Technology Co., Ltd.
Category: otc | Type: HUMAN OTC DRUG LABEL
Date: 20200414

ACTIVE INGREDIENTS: POLIHEXANIDE 0.4 g/100 mL
INACTIVE INGREDIENTS: CITRIC ACID MONOHYDRATE; ALCOHOL; WATER

Disposable Spray Disinfectant

Active Ingredients

Polyhexamethylene biguanidine(0.4%).

Purpose

Antimicrobial disinfectant

Warnings

Store in a cool, dry,well-ventilated and clean room with relative humidity not exceeding

80% and no corrosive gases.

Directions

1,Total skin disinfection:apply directly to skin,either by spraying or wiping, for 1 minute

2,Mucous membrane disinfection(not suitable for use on vaginal mucosa) ;

2.1,Rinse oral cavity using the undiluted solution for 1 minute.Rinse mouth out with water after disinfecting.

2.2,Apply directly to the membrane and rub into the surface for one minute.

3, Hand sanitizing：Apply directly to hands,either by spraying or wiping, and rub in for 1 minute.

4,Hand sanitizing for surgical purposes：Apply directly to hands, either by spraying, wiping, or soaking in the undiluted solution, for 3 minutes.

5,Disinfecting the surfaces of objects：Apply directly to the surface, either by spraying or wiping, for 10 minutes.

Other information

1, If there is any precipitation observed as a result of the storage process, this is a normal phenomenon and does not affect the product's efficacy.

2, For external use only,oral administration is strictly prohibited.

3,Please keep the product out of reach of children.

4, When used for mucous membrane disinfection,this should be limited to diagnosis and treatment inside medical institutions.

5, Do not use if any allergies against polyhexamethylene biguanidene are known, people with allergies should use with caution.

6,This product cannot be used together with soap or other anionic detergents.

7, This product has a moderately corrosive effect on carbon steel, but is suitable for the disinfection of copper,

stainless steel,aluminum, and ceramic surfaces.

INACTIVE INGREDIENTS

Water,citric acid,aromatics,alcohol.